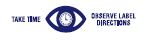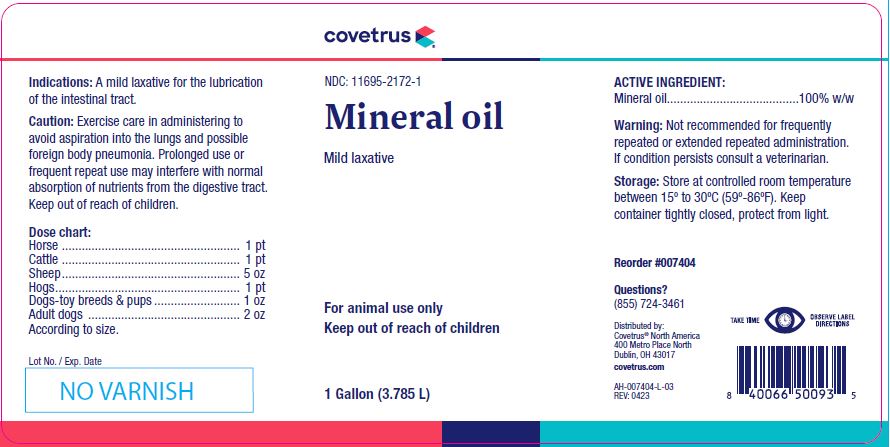 DRUG LABEL: Mineral oil
NDC: 11695-2172 | Form: LIQUID
Manufacturer: Butler Animal health Supply, LLC dba Covetrus North America
Category: animal | Type: OTC ANIMAL DRUG LABEL
Date: 20250808

ACTIVE INGREDIENTS: MINERAL OIL 854.5 g/1 L

Mineral oil

PURPOSE

Mild laxative

KEEP OUT OF REACH OF CHILDREN

For animal use only
Keep out of reach of children

HOW SUPPLIED

1 Gallon (3.785 L)

Indications:

A mild laxative for the lubrication of the intestinal tract.

Caution:

Exercise care in administering to avoid aspiration into the lungs and possible foreign body pneumonia. Prolonged use or frequent repeat use may interfere with normal absorption of nutrients from the digestive tract. Keep out of reach of children.

Dose chart:

Horse ...................................................... 1 pt
Cattle ...................................................... 1 pt
Sheep...................................................... 5 oz
Hogs........................................................ 1 pt
Dogs-toy breeds & pups ..........................1 oz
Adult dogs .............................................. 2 oz
According to size.

ACTIVE INGREDIENT:

Mineral oil........................................100% w/w

Warning:

Not recommended for frequently repeated or extended repeated administration. If condition persists, consult a veterinarian.

Storage:

Store at controlled room temperature between 15º to 30ºC (59º-86ºF). Keep container tightly closed, protect from light.

INFORMATION FOR OWNERS/CAREGIVERS

Reorder #007404

Questions?
(855) 724-3461

Distributed by:
Covetrus® North America
400 Metro Place North
Dublin, OH 43017
covetrus.com

AH-007404-L-03
REV: 0423